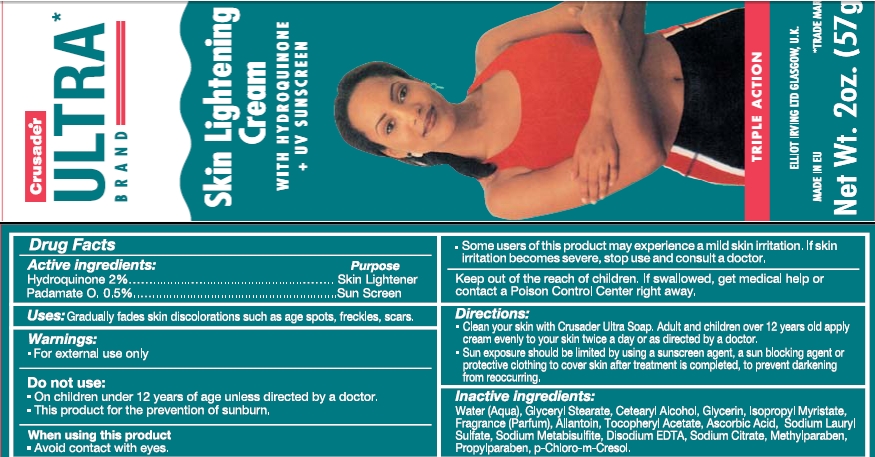 DRUG LABEL: Crusader Ultra Skin Lightening
NDC: 66129-210 | Form: CREAM
Manufacturer: International Beauty Exchange
Category: otc | Type: HUMAN OTC DRUG LABEL
Date: 20110601

ACTIVE INGREDIENTS: HYDROQUINONE 1.14 g/57 g; PADIMATE O .285 g/57 g
INACTIVE INGREDIENTS: WATER; GLYCERYL STEARATE CITRATE; CETOSTEARYL ALCOHOL; GLYCERIN; ISOPROPYL MYRISTATE; ALLANTOIN; ASCORBIC ACID; SODIUM METABISULFITE; SODIUM CITRATE; SODIUM LAURYL SULFATE; EDETATE DISODIUM; METHYLPARABEN; PROPYLPARABEN; CHLOROCRESOL

Drug Facts

ACTIVE INGREDIENT

Hydroquinone 2%

Padimate O, 0.5%

WARNINGS

For external use only

DO NOT USE

On children under 12 years of age unless directed by a doctor

WHEN USING

Avoid contact with eyes.

PURPOSE

Skin Lightener